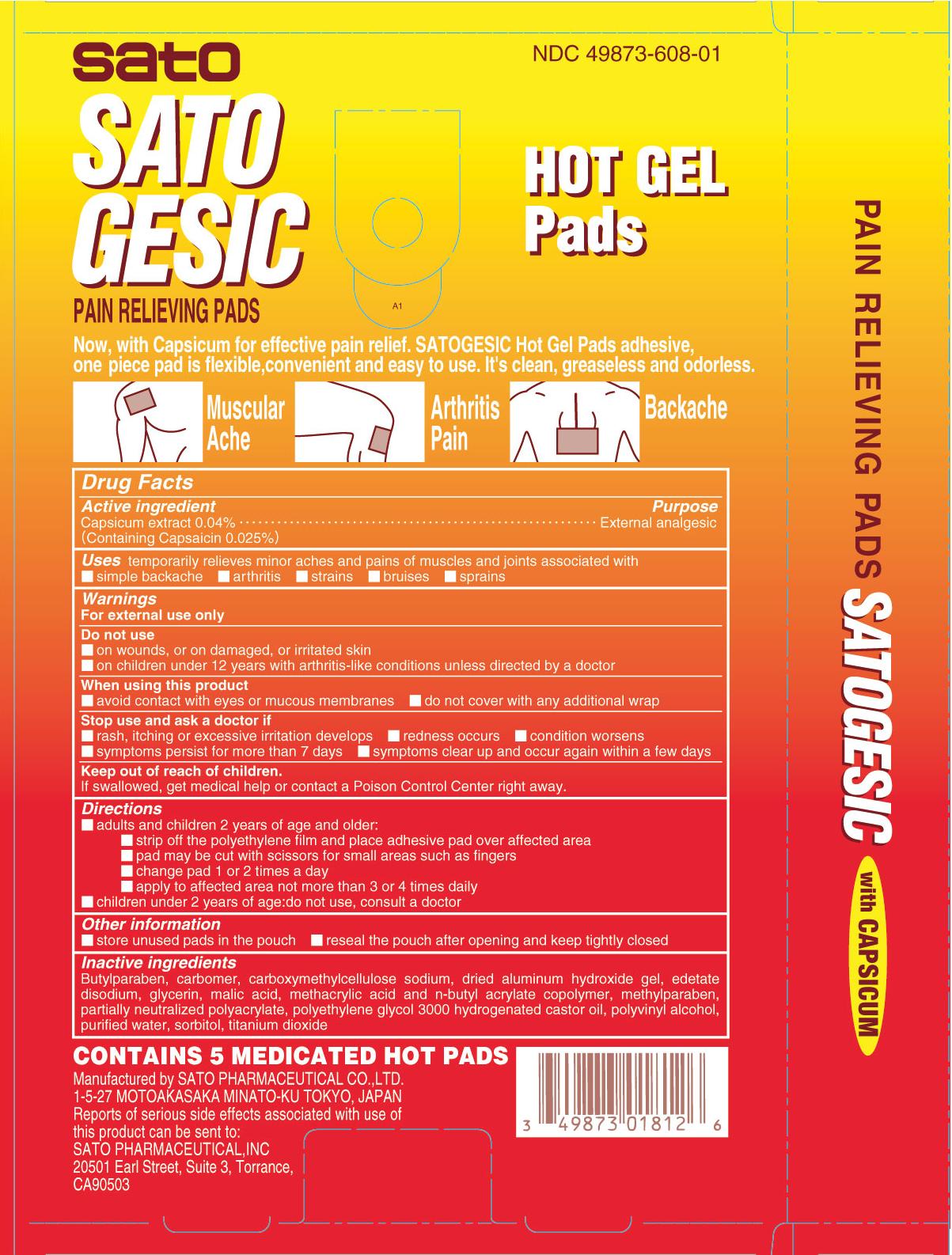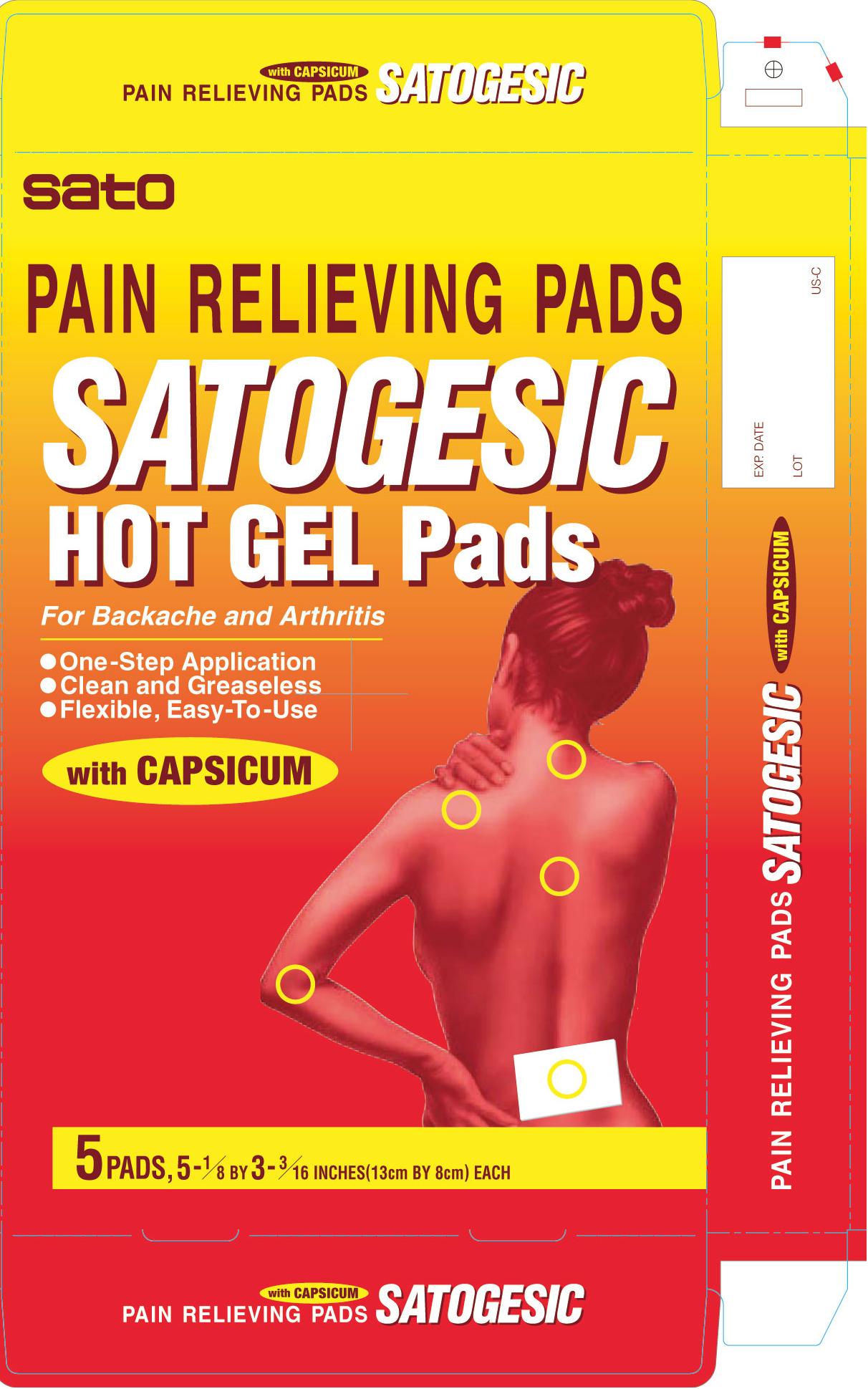 DRUG LABEL: Satogesic Hot
NDC: 49873-608 | Form: PATCH
Manufacturer: Sato Pharmaceutical Co., Ltd.
Category: otc | Type: HUMAN OTC DRUG LABEL
Date: 20231110

ACTIVE INGREDIENTS: CAPSAICIN 0.25 mg/1 1
INACTIVE INGREDIENTS: BUTYL ACRYLATE/METHACRYLIC ACID COPOLYMER (2% METHACRYLIC ACID); CARBOXYMETHYLCELLULOSE SODIUM; POLYVINYL ALCOHOL; SORBITOL; GLYCERIN; TITANIUM DIOXIDE; EDETATE DISODIUM; ALGELDRATE; MALIC ACID; WATER; BUTYLPARABEN; METHYLPARABEN; POLYOXYL 60 HYDROGENATED CASTOR OIL; CARBOMER INTERPOLYMER TYPE B (ALLYL PENTAERYTHRITOL CROSSLINKED); ACRYLIC ACID/SODIUM ACRYLATE COPOLYMER (1:1; 600 MPA.S AT 0.2%)

DRUG FACTS

Active ingredient
Capsicum extract 0.04% (Containing Capsaicin 0.025%)

Purpose
Capsaicin External analgesic

INDICATIONS AND USAGE

Uses temporary relieves minor aches and pains of muscles and joints associated with
■ simple backache ■ arthritis ■ strains ■ bruises ■ sprains

Warnings
For external use only

Do not use
■ on wounds, or on damaged, or irritated skin
■ on children under 12 years with arthritis-like conditions unless directed by a doctor

When using this product
■ avoid contact with eyes or mucous membranes ■ do not cover with any additional wrap

Stop use and ask a doctor if
■ rash, itching or excessive irritation develops ■ redness occurs ■ condition worsens
■ symptoms persist for more than 7 days ■ symptoms clear up and occur again withn a few days

Keep out of reach of children. If swallowed, get medical help or contact a Poison Control Center right away.

Other information
■ store unused pads in the pouch ■ reseal the pouch after opening and keep tightly closed

Directions

■ Adults and children 2 years of age and over:

■ strip off the polyethylene film and place adhesive pad over affected area

■ pad may be cut with scissors for small areas such as fingers

■ change pad 1 or 2 times a day

■ apply to affected area not more than 3 or 4 times daily

■ Children under 2 years of age: do not use, consult a doctor

Inactive ingredients
Butylparaben, carbomer, carboxymethylcellulose sodium, dried aluminum hydroxide gel, edetate disodium, glycerin, malic acid, methacrylic acid and n-butyl acrylate copolymer, methylparaben, partially neutralized polyacrylate, polyethylene glycol 3000 hydrogenated castor oil, polyvinyl alcohol, purified water, sorbitol, titanium dioxide